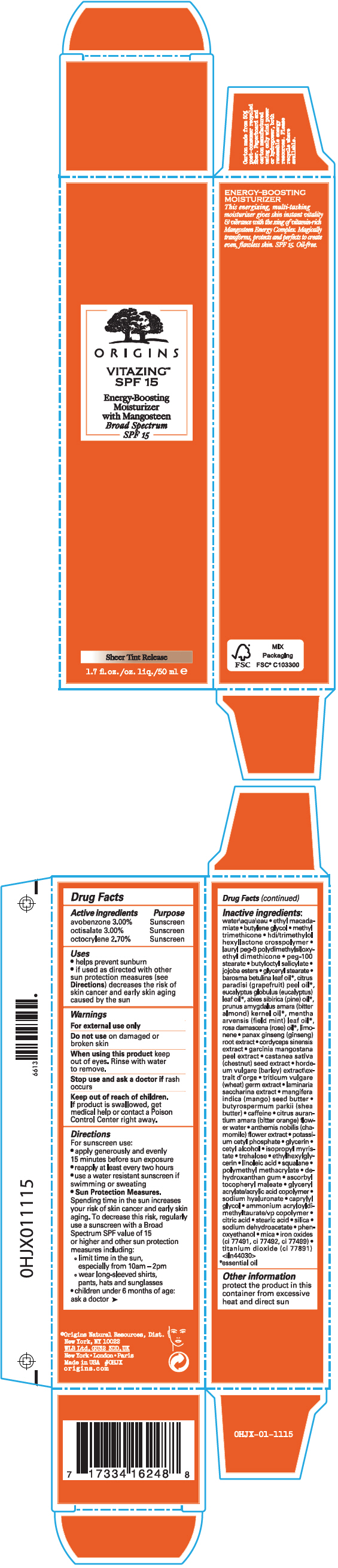 DRUG LABEL: VITAZING SPF 15 ENERGY BOOSTING MOISTURIZER WITH MANGOSTEEN BROAD SPECTRUM SPF 15
NDC: 59427-013 | Form: CREAM
Manufacturer: ORIGINS NATURAL RESOURCES INC.
Category: otc | Type: HUMAN OTC DRUG LABEL
Date: 20241225

ACTIVE INGREDIENTS: AVOBENZONE 30 mg/1 mL; OCTISALATE 30 mg/1 mL; OCTOCRYLENE 27 mg/1 mL
INACTIVE INGREDIENTS: WATER; ETHYL MACADAMIATE; BUTYLENE GLYCOL; METHYL TRIMETHICONE; HEXAMETHYLENE DIISOCYANATE/TRIMETHYLOL HEXYLLACTONE CROSSPOLYMER; LAURYL PEG-9 POLYDIMETHYLSILOXYETHYL DIMETHICONE; PEG-100 STEARATE; BUTYLOCTYL SALICYLATE; GLYCERYL MONOSTEARATE; AGATHOSMA BETULINA LEAF OIL; GRAPEFRUIT OIL; EUCALYPTUS OIL; WHITE PINE OIL; BITTER ALMOND OIL; MENTHA ARVENSIS LEAF OIL; ROSE OIL; ASIAN GINSENG; BARLEY; WHEAT; MANGIFERA INDICA SEED BUTTER; SHEA BUTTER; CAFFEINE; BITTER ORANGE; CHAMOMILE; POTASSIUM CETYL PHOSPHATE; GLYCERIN; CETYL ALCOHOL; ISOPROPYL MYRISTATE; TREHALOSE; ETHYLHEXYLGLYCERIN; LINOLEIC ACID; SQUALANE; POLY(METHYL METHACRYLATE; 450000 MW); DEHYDROXANTHAN GUM; ASCORBYL TOCOPHERYL MALEATE; HYALURONATE SODIUM; CAPRYLYL GLYCOL; AMMONIUM ACRYLOYLDIMETHYLTAURATE/VP COPOLYMER; CITRIC ACID MONOHYDRATE; STEARIC ACID; SILICON DIOXIDE; SODIUM DEHYDROACETATE; PHENOXYETHANOL; MICA; FERRIC OXIDE RED; FERRIC OXIDE YELLOW; FERROSOFERRIC OXIDE; TITANIUM DIOXIDE

VITAZING™ SPF 15 ENERGY BOOSTING MOISTURIZER WITH MANGOSTEEN BROAD SPECTRUM SPF 15

Drug Facts

ACTIVE INGREDIENT

Active ingredients | Purpose
avobenzone 3.00% | Sunscreen
octisalate 3.00% | Sunscreen
octocrylene 2.70% | Sunscreen

Uses

- helps prevent sunburn
- if used as directed with other sun protection measures (see Directions) decreases the risk of skin cancer and early skin aging caused by the sun

Warnings

For external use only

Do not use on damaged or broken skin

When using this product keep out of eyes. Rinse with water to remove.

Stop use and ask a doctor if rash occurs

Keep out of reach of children. If product is swallowed, get medical help or contact a Poison Control Center right away.

Directions

For sunscreen use:

- apply generously and evenly 15 minutes before sun exposure
- reapply at least every two hours
- use a water resistant sunscreen if swimming or sweating
- Sun Protection Measures. Spending time in the sun increases your risk of skin cancer and early skin aging. To decrease this risk, regularly use a sunscreen with a Broad Spectrum SPF value of 15 or higher and other sun protection measures including:
  - limit time in the sun, especially from 10am – 2pm
  - wear long-sleeved shirts, pants, hats and sunglasses
- children under 6 months of age: ask a doctor

Inactive ingredients

water\aqua\eau • ethyl macadamiate • butylene glycol • methyl trimethicone • hdi/trimethylol hexyllactone crosspolymer • lauryl peg-9 polydimethylsiloxyethyl dimethicone • peg-100 stearate • butyloctyl salicylate • jojoba esters • glyceryl stearate • barosma betulina leaf oil [essential oil] , citrus paradisi (grapefruit) peel oil , eucalyptus globulus (eucalyptus) leaf oil , abies sibirica (pine) oil , prunus amygdalus amara (bitter almond) kernel oil , mentha arvensis (field mint) leaf oil , rosa damascena (rose) oil , limonene • panax ginseng (ginseng) root extract • cordyceps sinensis extract • garcinia mangostana peel extract • castanea sativa (chestnut) seed extract • hordeum vulgare (barley) extract\extrait d'orge • triticum vulgare (wheat) germ extract • laminaria saccharina extract • mangifera indica (mango) seed butter • butyrospermum parkii (shea butter) • caffeine • citrus aurantium amara (bitter orange) flower water • anthemis nobilis (chamomile) flower extract • potassium cetyl phosphate • glycerin • cetyl alcohol • isopropyl myristate • trehalose • ethylhexylglycerin • linoleic acid • squalane • polymethyl methacrylate • dehydroxanthan gum • ascorbyl tocopheryl maleate • glyceryl acrylate/acrylic acid copolymer • sodium hyaluronate • caprylyl glycol • ammonium acryloyldimethyltaurate/vp copolymer • citric acid • stearic acid • silica • sodium dehydroacetate • phenoxyethanol • mica • iron oxides (ci 77491, ci 77492, ci 77499) • titanium dioxide (ci 77891) <iln44030>

Other information

protect the product in this container from excessive heat and direct sun

PRINCIPAL DISPLAY PANEL - 50 ml Tube Carton

ORIGINS

VITAZING™
SPF 15

Energy-Boosting
Moisturizer
with Mangosteen
Broad Spectrum
SPF 15

Sheer Tint Release

1.7 fl. oz./oz. liq./50 ml e